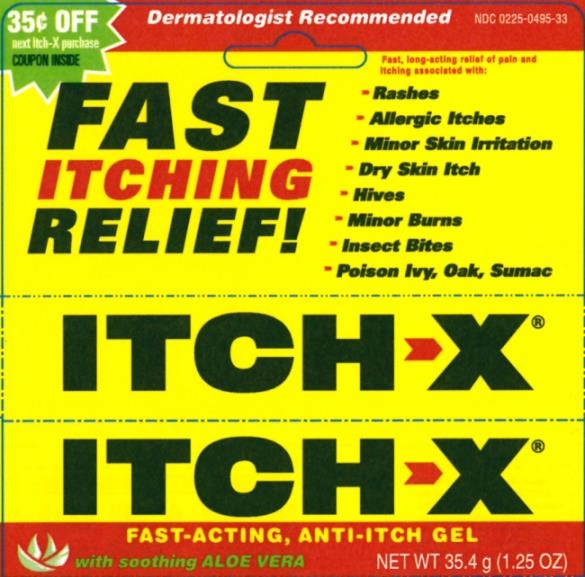 DRUG LABEL: ITCH X
NDC: 0225-0495 | Form: GEL
Manufacturer: BF ASCHER AND CO INC
Category: otc | Type: HUMAN OTC DRUG LABEL
Date: 20241205

ACTIVE INGREDIENTS: BENZYL ALCOHOL 10 g/100 g; PRAMOXINE HYDROCHLORIDE 1 g/100 g
INACTIVE INGREDIENTS: BUTYLENE GLYCOL; ALCOHOL; ALOE; WATER; EDETOL; CARBOMER HOMOPOLYMER TYPE B (ALLYL SUCROSE CROSSLINKED); DIAZOLIDINYL UREA; FD&C BLUE NO. 1; SODIUM BENZOATE; SODIUM SULFITE; POTASSIUM SORBATE; IODOPROPYNYL BUTYLCARBAMATE; CITRIC ACID MONOHYDRATE; STYRENE/AMMONIUM ACRYLATE COPOLYMER (300000 MW)

Itch-X Gel

Active ingredients......................................Purpose

Benzyl alcohol 10%......................................Topical analgesic
Pramoxine hydrochloride 1%.......................Topical analgesic

Use

Temporarily relieves pain and itching associated with insect bites, minor burns, sunburn, minor cuts, scrapes, minor skin irritations, hives and rashes due to poison ivy, poison oak, or poison sumac

Use

Temporarily relieves pain and itching associated with insect bites, minor burns, sunburn, minor cuts, scrapes, minor skin irritations, hives and rashes due to poison ivy, poison oak, or poison sumac

Warnings

- For external use only.
- Avoid contact with eyes.

Do not use

- on open wounds, damaged, or blistered skin.
- for vaginal, genital, or rectal itching.
- on children under 2 years of age unless under the advice and supervision of a physician.

Stop use and ask a doctor if condition worsens, or if symptoms persist for more than 7 days or clear up and occur again within a few days.

Stop use and ask a doctor if condition worsens, or if symptoms persist for more than 7 days or clear up and occur again within a few days.

PREGNANCY OR BREAST FEEDING

If pregnant or breast-feeding, ask a health professional before use.

KEEP OUT OF REACH OF CHILDREN

Keep this and all drugs out of reach of children. In case of ingestion, get medical help or contact a poison control center immediately.

Directions

- adults and children 2 years and older - apply to affected area not more than 3 or 4 times daily
- children under 2 years - consult a physician

Other information

- store at 59°-86° F (15°-30° C) in a dry place
- mfd. in the USA for B.F. Ascher & Co., Inc.

INACTIVE INGREDIENT

Inactive ingredients: aloe barbadensis leaf juice (aloe vera gel), blue 1, butylene glycol, carbomer, citric acid, diazolidinyl urea, iodopropynyl butylcarbamate, potassium sorbate, SD alcohol 40, sodium benzoate, sodium sulfite, styrene/acrylates copolymer, tetrahydroxypropyl ethylenediamine, and water

QUESTIONS

Questions? Call 1-800-324-1880, 7:30am - 4:00pm Central, M - F, or visit bfascher.com

PACKAGE LABEL

Itch-X Gel PDP